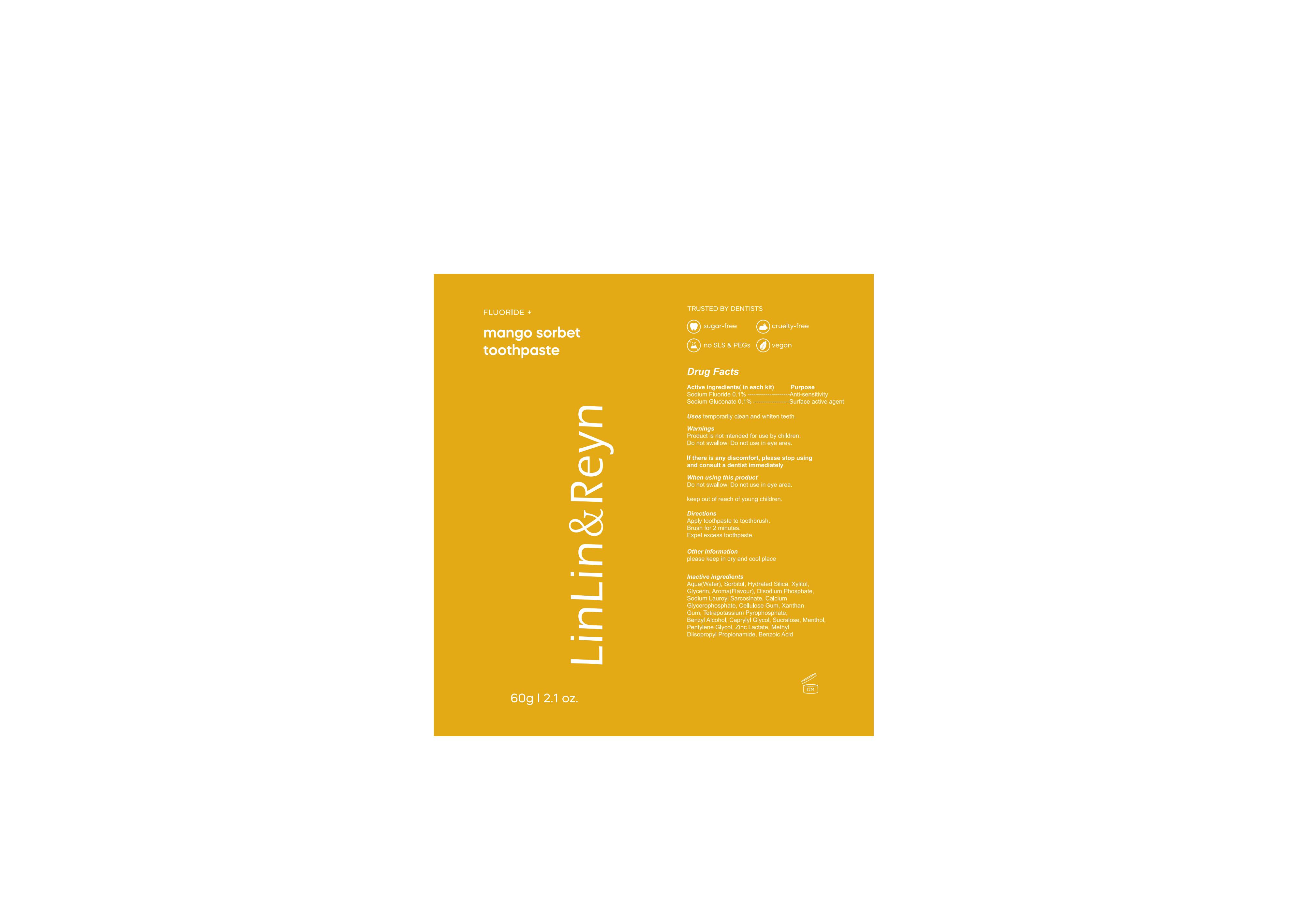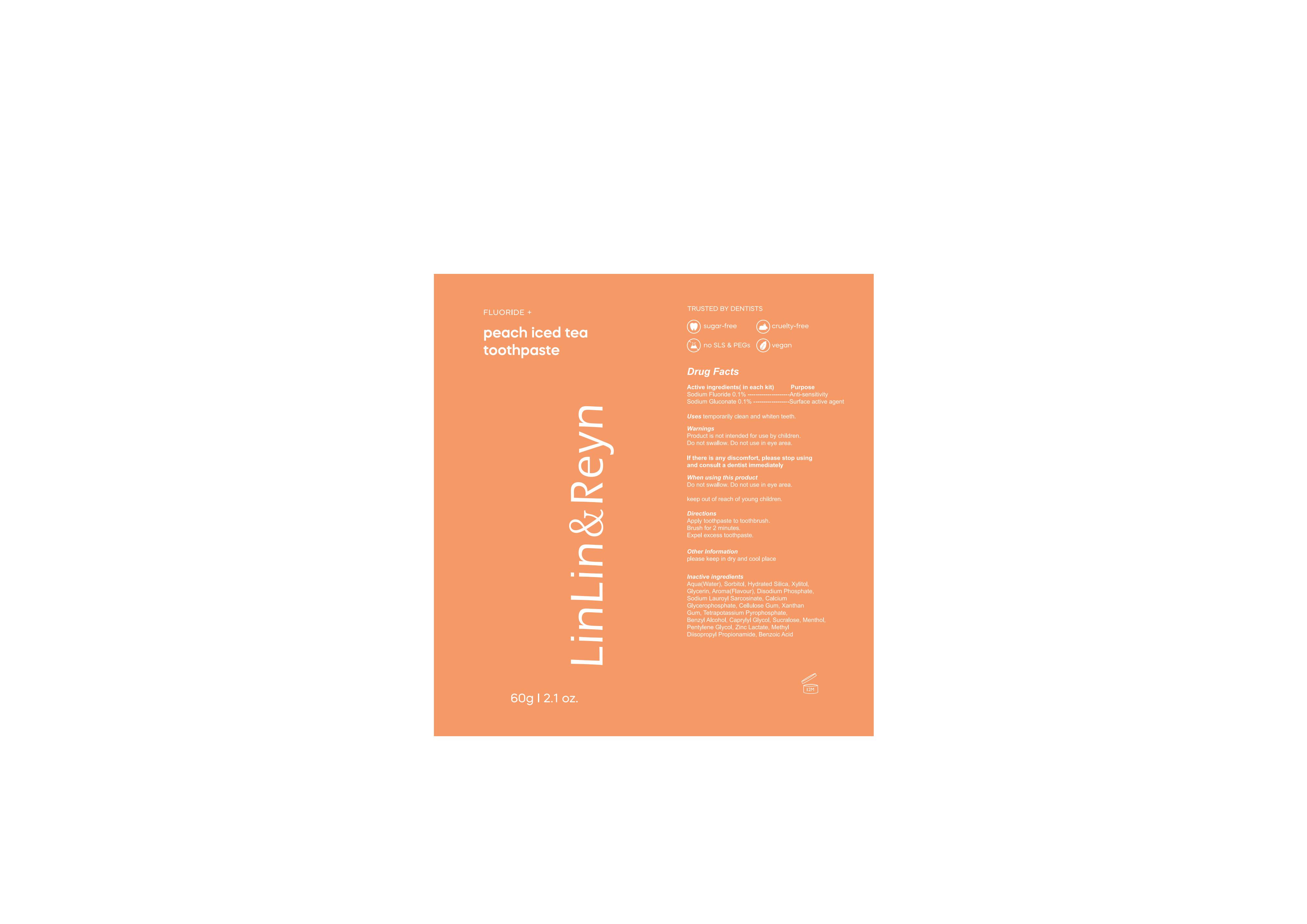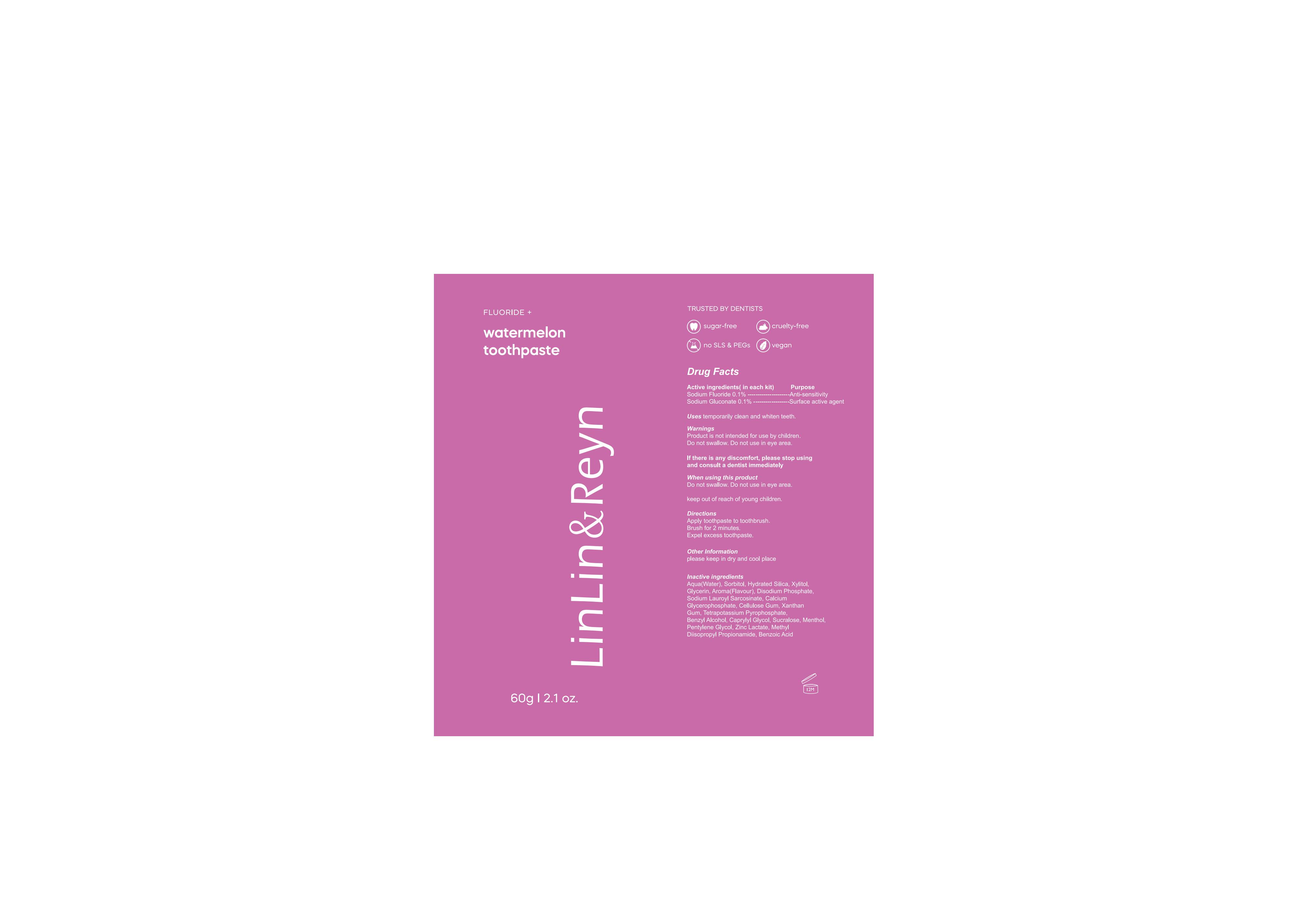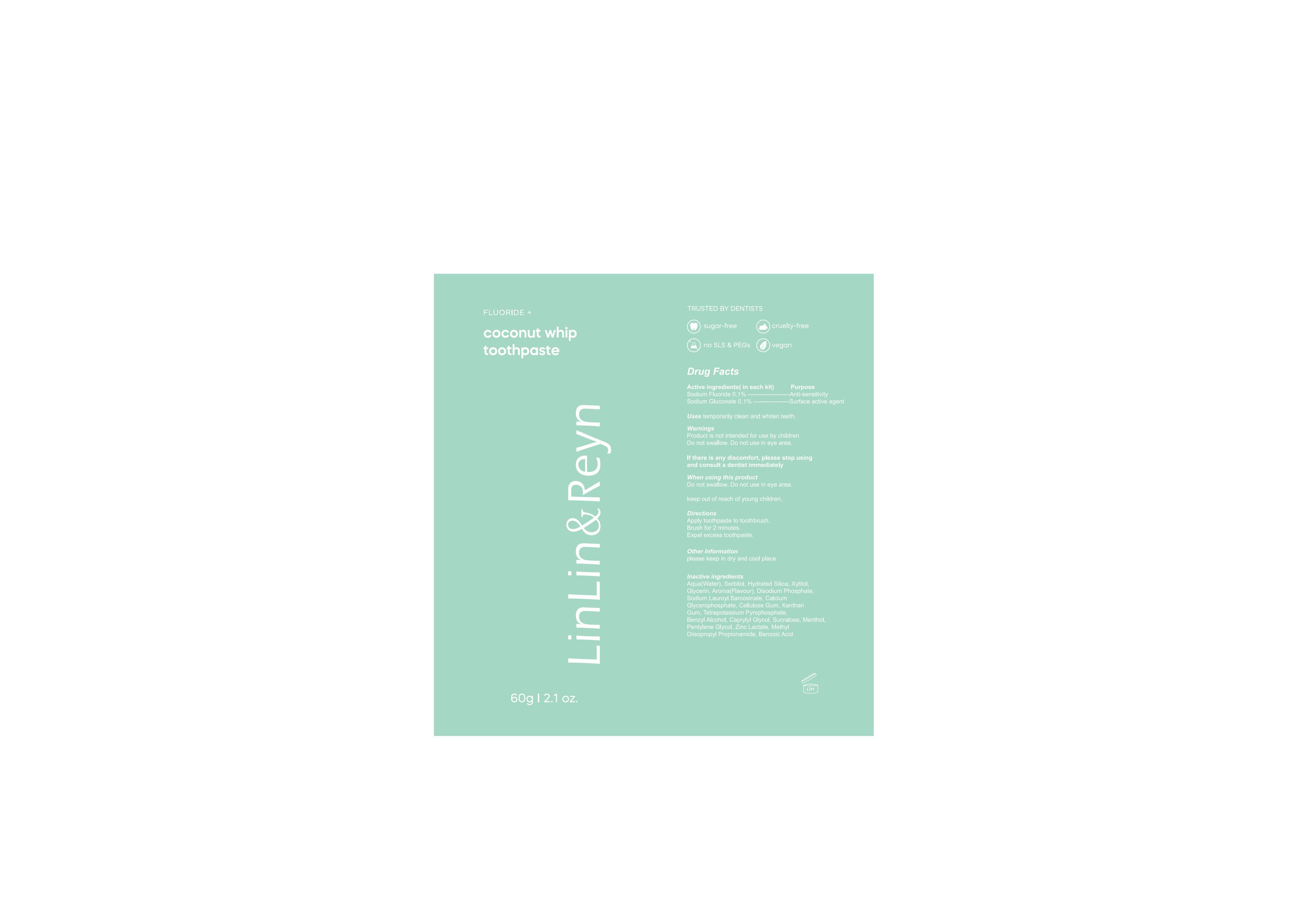 DRUG LABEL: GlorySmile toothpaste.
NDC: 83812-003 | Form: CREAM
Manufacturer: LLRN PERSONAL CARE(SHENZHEN)CO., LTD
Category: otc | Type: HUMAN OTC DRUG LABEL
Date: 20231123

ACTIVE INGREDIENTS: SODIUM FLUORIDE 0.1 g/100 g; SODIUM GLUCONATE 0.1 g/100 g
INACTIVE INGREDIENTS: XANTHAN GUM; PENTYLENE GLYCOL; METHYL DIISOPROPYL PROPIONAMIDE; WATER; GLYCERIN; CAPRYLYL GLYCOL; SUCRALOSE; ZINC LACTATE; SODIUM LAUROYL SARCOSINATE; CALCIUM GLYCEROPHOSPHATE; HYDRATED SILICA; SODIUM PHOSPHATE, DIBASIC, ANHYDROUS; BENZYL ALCOHOL; BENZOIC ACID; SORBITOL; XYLITOL; CARBOXYMETHYLCELLULOSE SODIUM, UNSPECIFIED FORM; POTASSIUM PYROPHOSPHATE; MENTHOL

Active Ingredient

Sodium Fluoride 0.1%

Sodium Gluconate 0.1%

Purpose

teeth cleaning, anti-sensitivity

Use

Those who want to clean and whiten their teeth.

Warnings

Product is not intended for use by children. Do not swallow. Do not use in eye area.

Do not use

Product is not intended for use by children.

When Using

Do not swallow. Do not use in eye area.

Stop Use

If there is any discomfort, please stop using.

Ask Doctor

If there is any discomfort, please consult a dentist immediately

Keep Oot Of Reach Of Children

keep out of reach of young children

Directions

Apply toothpaste to toothbrush. Brush for 2 minutes. Expel excess toothpaste.

Other information

please keep in dry and cool place

Inactive ingredients

Aqua(Water)、Sorbitol、Hydrated Silica、Xylitol、Glycerin 、Aroma(Flavour)、Disodium Phosphate、Sodium Lauroyl Sarcosinate、Calcium Glycerophosphate、Cellulose Gum、Xanthan Gum、Tetrapotassium Pyrophosphate、Benzyl Alcohol、Caprylyl Glycol、Sucralose、Menthol、Pentylene Glycol、Zinc Lactate、Methyl Diisopropyl Propionamide、Benzoic Acid